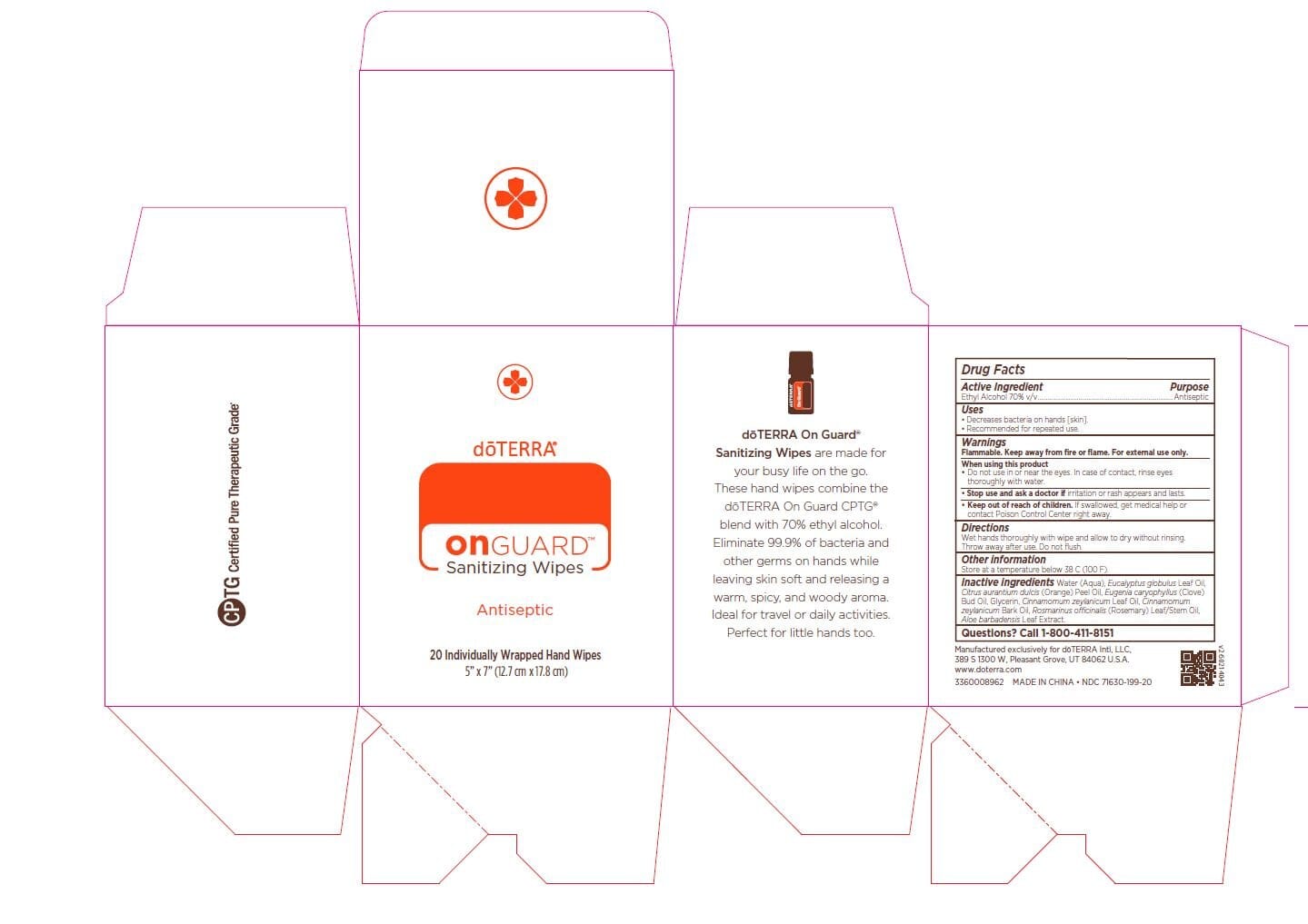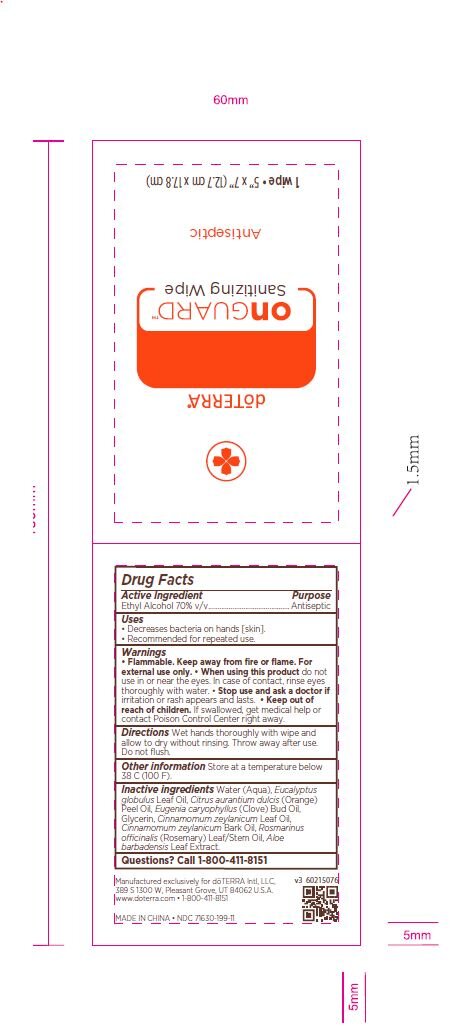 DRUG LABEL: On Guard Sanitizing Wipes
NDC: 71630-199 | Form: CLOTH
Manufacturer: doTERRA International, LLC
Category: otc | Type: HUMAN OTC DRUG LABEL
Date: 20220131

ACTIVE INGREDIENTS: ALCOHOL 70 mL/100 mL
INACTIVE INGREDIENTS: EUCALYPTUS OIL; WATER; GLYCERIN; CINNAMON LEAF OIL; ROSEMARY OIL; CLOVE OIL; CINNAMON BARK OIL; ALOE VERA LEAF; ORANGE OIL

On Guard Sanitizing Wipes (V1-V)

Active Ingredient(s)

Ethyl Alcohol 70% v/v. Purpose: Antiseptic

Purpose

Antiseptic, Hand Sanitizer

Use

•Decreases bacteria on hands [skin].
•Recommended for repeated use.

Warnings

For external use only. Flammable. Keep away from heat or flame

Do not use in or near the eyes. In case of contact, rinse eyes thoroughly with water

Stop use and ask a doctor if irritation or rash appears and lasts.

Keep out of reach of children. If swallowed, get medical help or contact Poison Control Center right away.

Stop use and ask a doctor if irritation or rash occurs and lasts.

Keep out of reach of children. If swallowed, get medical help or contact a Poison Control Center right away.

Directions

Wet hands thoroughly with wipe and allow to dry without rinsing. Throw away after use. Do not flush.

Other information

- Store at a temperature below 38 C (100 F).

Inactive ingredients

Water (Aqua), Eucalyptus globulus Leaf Oil, Citrus aurantium dulcis (Orange) Peel Oil, Eugenia caryophyllus (Clove) Bud Oil, Glycerin, Cinnamomum zeylanicum Leaf Oil, Cinnamomum zeylanicum Bark Oil, Rosmarinus officinalis (Rosemary) Leaf/Stem Oil,
Aloe barbadensis Leaf Extract.

Package Label - Principal Display Panel

20 Count NDC: 71630-199-20

Single Packet: NDC 71630-199-11